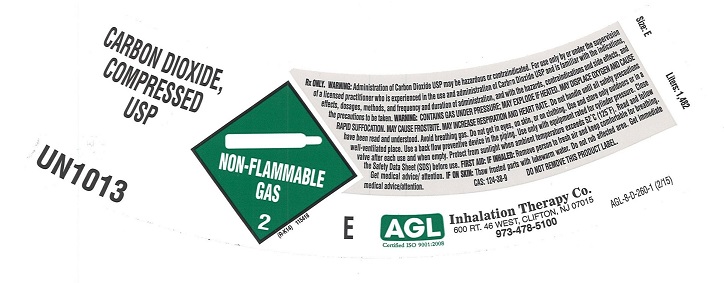 DRUG LABEL: Carbon Dioxide
NDC: 17575-104 | Form: GAS
Manufacturer: AGL Inhalation Therapy Co.
Category: prescription | Type: HUMAN PRESCRIPTION DRUG LABEL
Date: 20260101

ACTIVE INGREDIENTS: CARBON DIOXIDE 990 mL/1 L

carbon dioxide

PACKAGE LABEL

CARBON DIOXIDE, COMPRESSED USP UN1013 NON-FLAMMABLE GAS 2 Rx only
WARNING: Administration of Carbon Dioxide may be hazardous or contraindicated. For use only by or under the supervision of a licensed practitioner who is experienced in the use and administration of Carbon Dioxide and is familiar with the indications, effects, dosages, methods, and frequency and duration of administration, and with the hazards, contraindications, and side effects and the precautions to be taken. WARNING: CONTAINS GAS UNDER PRESSURE; MAY EXPLODE IF HEATED. MAY DISPLACE OXYGEN AND CAUSE RAPID SUFFOCATION. MAY CAUSE FROSTBITE. MAY INCREASE RESPIRATION AND HEART RATE. Do not handle until all safety precautions have been read and understood. Keep and store away from clothing and other combustible materials. Keep valves and fittings free from grease and oil. Use and store only outdoors or in a well-ventilated place. In case of fire: Stop leak if safe to do so. Use a back flow preventive device in the piping. Use only with equipment of compatible materials of construction and rated for cylinder pressure. Use only with equipment cleaned for oxygen service. Open valve slowly. Close valve after each use and when empty. Protect from sunlight when Protect from sunlight when ambient temperature exceeds 52 degrees C (125 degrees F). Read and follow the Safety Data Sheet (SDS) before use. FIRST AID: IF INHALED: Remove person to fresh air and keep comfortable for breathing. Get immediate medical advice/attention. IF ON SKIN: Thaw frosted parts with lukewarm water. Do not rub affected area. Get immediate medical advice/attention. CAS: 124-38-9 DO NOT REMOVE THIS PRODUCT LABEL. Size: E Liters: 1,482 E
AGL Certified ISO 9001:2008 Inhalation Therapy Co. 600 RT. 46 WEST, CLIFTON, NJ 07015 973-478-5100